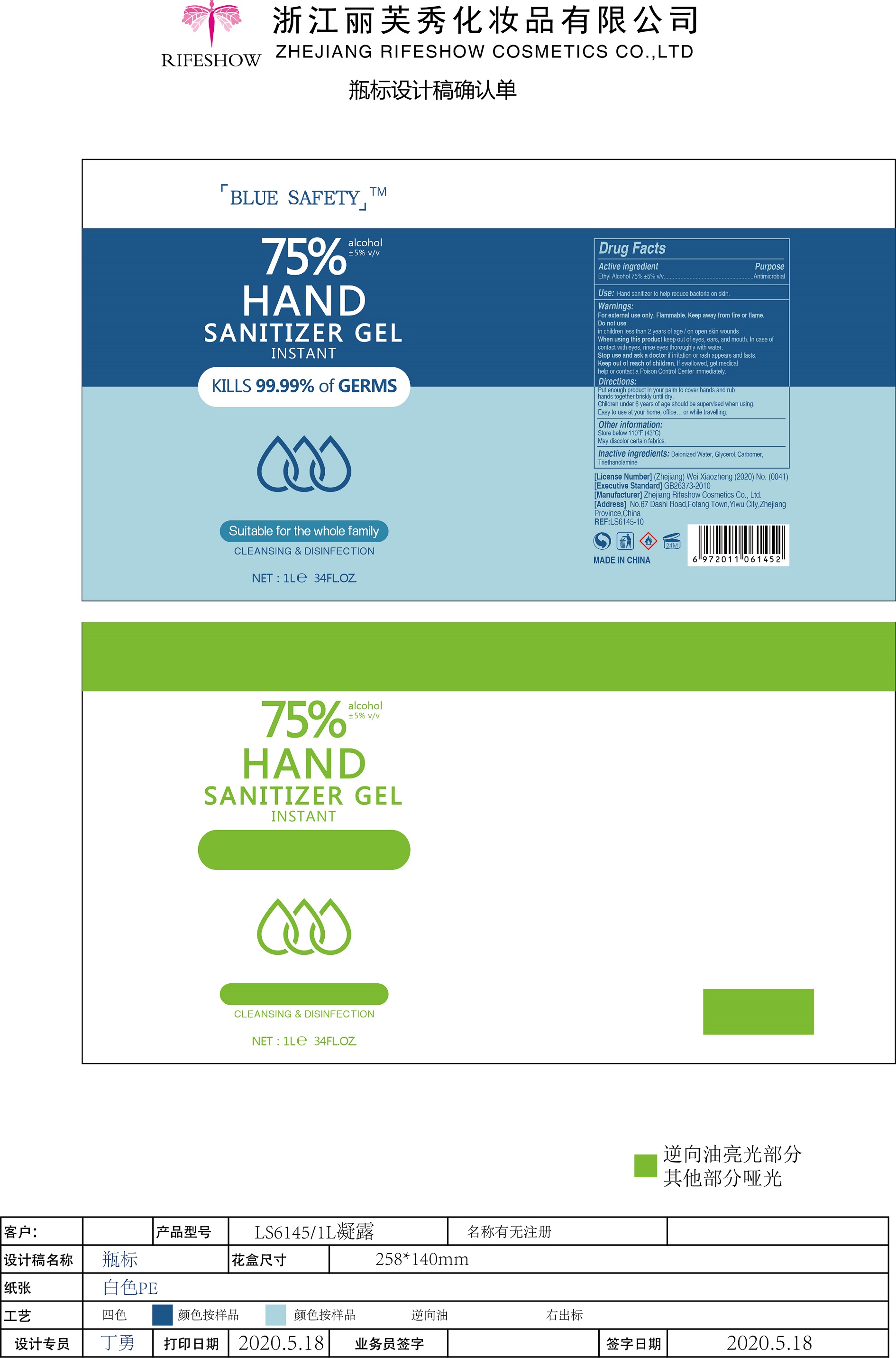 DRUG LABEL: Hand Sanitizer gel
NDC: 56084-019 | Form: GEL
Manufacturer: ZHEJIANG RIFESHOW COSMETICS CO.,LTD
Category: otc | Type: HUMAN OTC DRUG LABEL
Date: 20200730

ACTIVE INGREDIENTS: ALCOHOL 75 mL/100 mL
INACTIVE INGREDIENTS: TROLAMINE; GLYCERIN; CARBOMER HOMOPOLYMER, UNSPECIFIED TYPE; WATER

Active Ingredient(s)

Ethyl Alcohol 75%±5% v/v. Purpose: Antimicrobial

Purpose

Antimicrobial, Hand Sanitizer gel

Use

Hand Sanitizer to help reduce bacteria on skin

Warnings

For external use only. Flammable. Keep away from fire or flame

Do not use

- in children less than 2 months of age
- on open skin wounds

When using this product keep out of eyes, ears, and mouth. In case of contact with eyes, rinse eyes thoroughly with water.
Stop use and ask a doctor if irritation or rash appears and lasts
Keep out of reach of children. If swallowed, get medical help or contact a Poison Control Center immediately.

Stop use and ask a doctor if irritation or rash occurs. These may be signs of a serious condition.

Keep out of reach of children. If swallowed, get medical help or contact a Poison Control Center right away.

Other information

Store between 110℉(43℃)

May discolor certain fabrics

Inactive ingredients

Deionized water,Glycerol, carbome,Trithanolamine

Direction

Put enough product in your palm to cover hands and rub hands together briskly until dry.Children under 6 years of age should be supervised when using.Easy to use at your home,office or while travelling